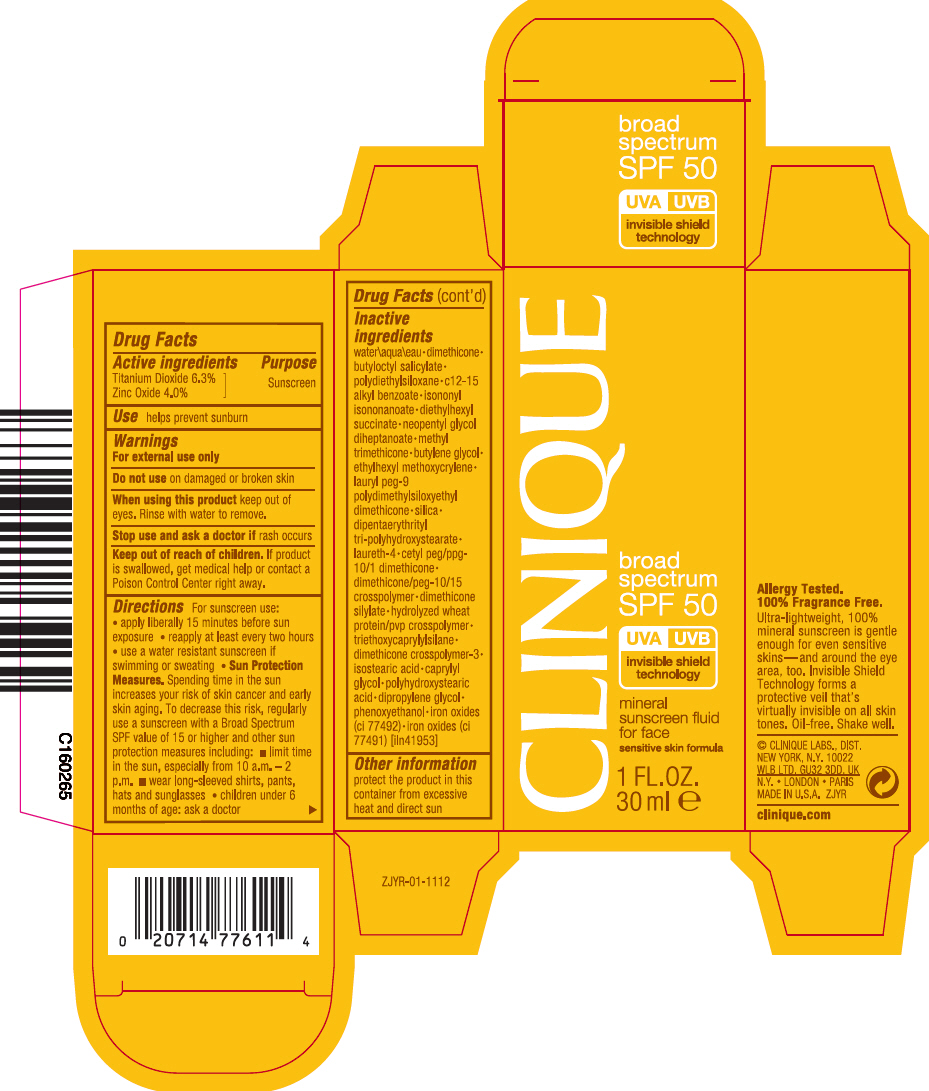 DRUG LABEL: CLINIQUE SPF 50 BROAD SPECTRUM MINERAL SUNSCREEN FLUID FOR FACE
NDC: 49527-752 | Form: LOTION
Manufacturer: CLINIQUE LABORATORIES LLC
Category: otc | Type: HUMAN OTC DRUG LABEL
Date: 20241225

ACTIVE INGREDIENTS: TITANIUM DIOXIDE 63 mg/1 mL; ZINC OXIDE 40 mg/1 mL
INACTIVE INGREDIENTS: WATER; DIMETHICONE; BUTYLOCTYL SALICYLATE; ALKYL (C12-15) BENZOATE; ISONONYL ISONONANOATE; DIETHYLHEXYL SUCCINATE; NEOPENTYL GLYCOL DIHEPTANOATE; METHYL TRIMETHICONE; BUTYLENE GLYCOL; ETHYLHEXYL METHOXYCRYLENE; LAURYL PEG-9 POLYDIMETHYLSILOXYETHYL DIMETHICONE; SILICON DIOXIDE; DIPENTAERYTHRITYL TRI-POLYHYDROXYSTEARATE; LAURETH-4; TRIETHOXYCAPRYLYLSILANE; ISOSTEARIC ACID; CAPRYLYL GLYCOL; DIPROPYLENE GLYCOL; PHENOXYETHANOL; FERRIC OXIDE YELLOW; FERRIC OXIDE RED

CLINIQUE SPF 50 BROAD SPECTRUM MINERAL SUNSCREEN FLUID FOR FACE

Drug Facts

Active ingredients

Titanium Dioxide 6.3%

Zinc Oxide 4.0%

Purpose

Sunscreen

Use

helps prevent sunburn

Warnings

For external use only

Do not use on damaged or broken skin

When using this product keep out of eyes. Rinse with water to remove.

Stop use and ask a doctor if rash occurs

Keep out of reach of children. If product is swallowed, get medical help or contact a Poison Control Center right away.

Directions

For sunscreen use:

- apply liberally 15 minutes before sun exposure
- reapply at least every two hours
- use a water resistant sunscreen if swimming or sweating
- Sun Protection Measures. Spending time in the sun increases your risk of skin cancer and early skin aging. To decrease this risk, regularly use a sunscreen with a Broad Spectrum SPF value of 15 or higher and other sun protection measures including:
  - limit time in the sun, especially from 10 a.m. – 2 p.m.
  - wear long-sleeved shirts, pants, hats and sunglasses
- children under 6 months of age: ask a doctor

Inactive ingredients

water\aqua\eau•dimethicone•butyloctyl salicylate•polydiethylsiloxane•c12-15 alkyl benzoate•isononyl isononanoate•diethylhexyl succinate•neopentyl glycol diheptanoate•methyl trimethicone•butylene glycol•ethylhexyl methoxycrylene•lauryl peg-9 polydimethylsiloxyethyl dimethicone•silica•dipentaerythrityl tri-polyhydroxystearate•laureth-4•cetyl peg/ppg-10/1 dimethicone•dimethicone/peg-10/15 crosspolymer•dimethicone silylate•hydrolyzed wheat protein/pvp crosspolymer•triethoxycaprylylsilane•dimethicone crosspolymer-3•isostearic acid•caprylyl glycol•polyhydroxystearic acid•dipropylene glycol•phenoxyethanol•iron oxides (ci 77492)•iron oxides (ci 77491) [iln41953]

Other information

protect the product in this container from excessive heat and direct sun

PRINCIPAL DISPLAY PANEL - 30 ml Bottle Carton

CLINIQUE

broad
spectrum
SPF 50

UVA
UVB
invisible shield
technology

mineral
sunscreen fluid
for face

sensitive skin formula

1 FL.OZ.
30 ml e